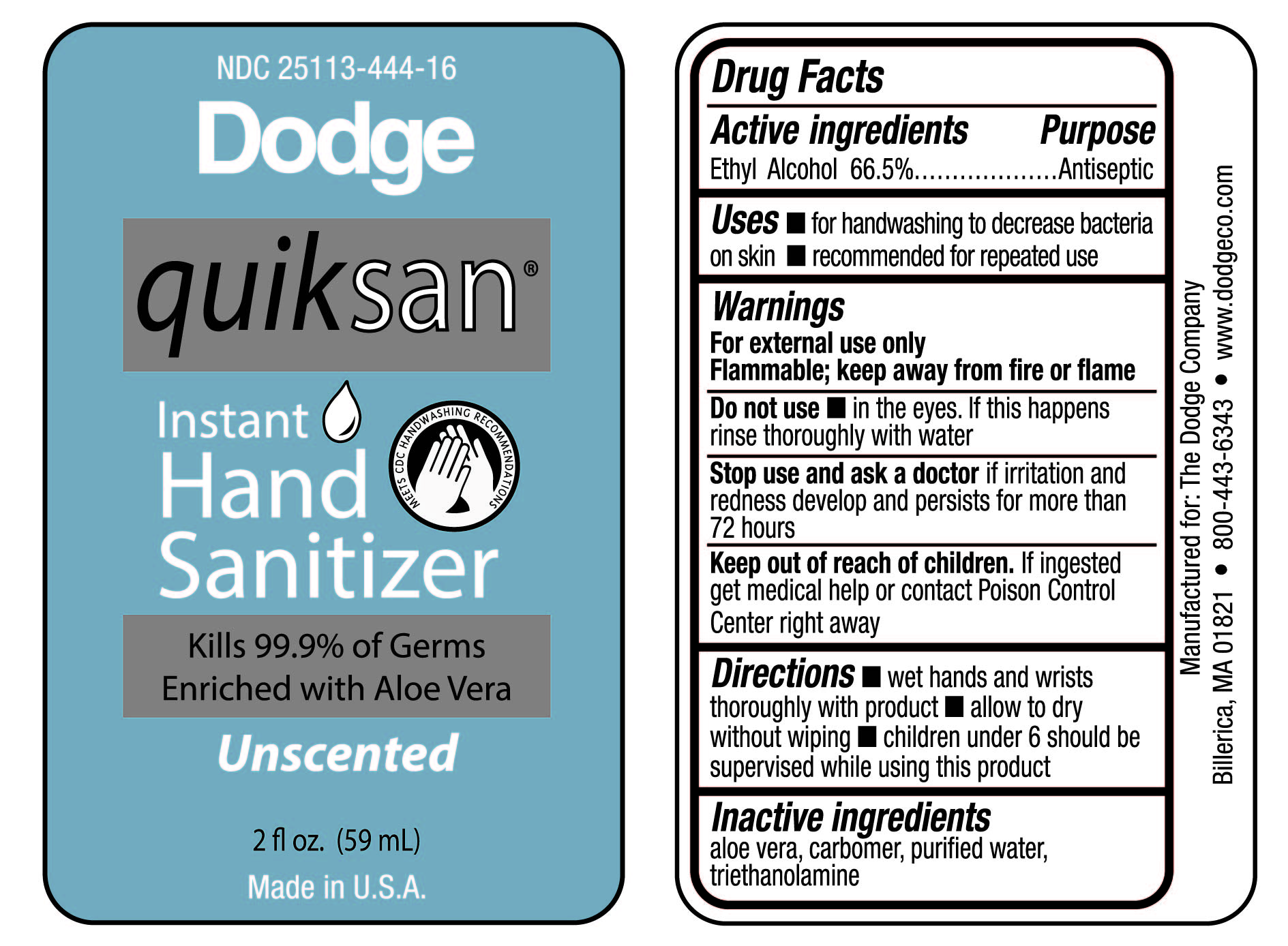 DRUG LABEL: Instant Hand Sanitizer
NDC: 25113-444 | Form: GEL
Manufacturer: Dodge
Category: otc | Type: HUMAN OTC DRUG LABEL
Date: 20241227

ACTIVE INGREDIENTS: ALCOHOL 665 mg/1 L
INACTIVE INGREDIENTS: ALOE VERA LEAF; CARBOMER INTERPOLYMER TYPE A (ALLYL SUCROSE CROSSLINKED); WATER; TROLAMINE

25113-444-16, Hand Sanitizer

Active ingredient

Ethyl Alcohol 66.5%

Purpose

Antiseptic

Uses

- for handwashing to decrease bacteria on skin
- recommended for repeated use

Warnings

For external use only. Flammable, keep away from fire or flame.

DO NOT USE

Do not usein the eyes. If this happens, rinse thoroughly with water

Stop use and ask a doctor ifirritation and redness develop and persists for more than 72 hours

Keep out of reach of children

If ingested get medical help or contact a Poison Control Center right away

Directions

- wet hands thoroughly with product
- allow to dry without wiping
- children under 6 should be supervised while using this product

Inactive ingredients

aloe vera, carbomer, purified water, triethanolamine

Principal Display Panel - 59 mL Bottle Label

NDC 25113-444-16

Dodge

quiksan®

Instant
Hand
Santizer

MEETS CDC HANDWASHING RECOMMENDATIONS

Kills 99.9% of Germs

Enriched with Aloe Vera

Unscented

2 fl oz (59mL)

Made in U.S.A.